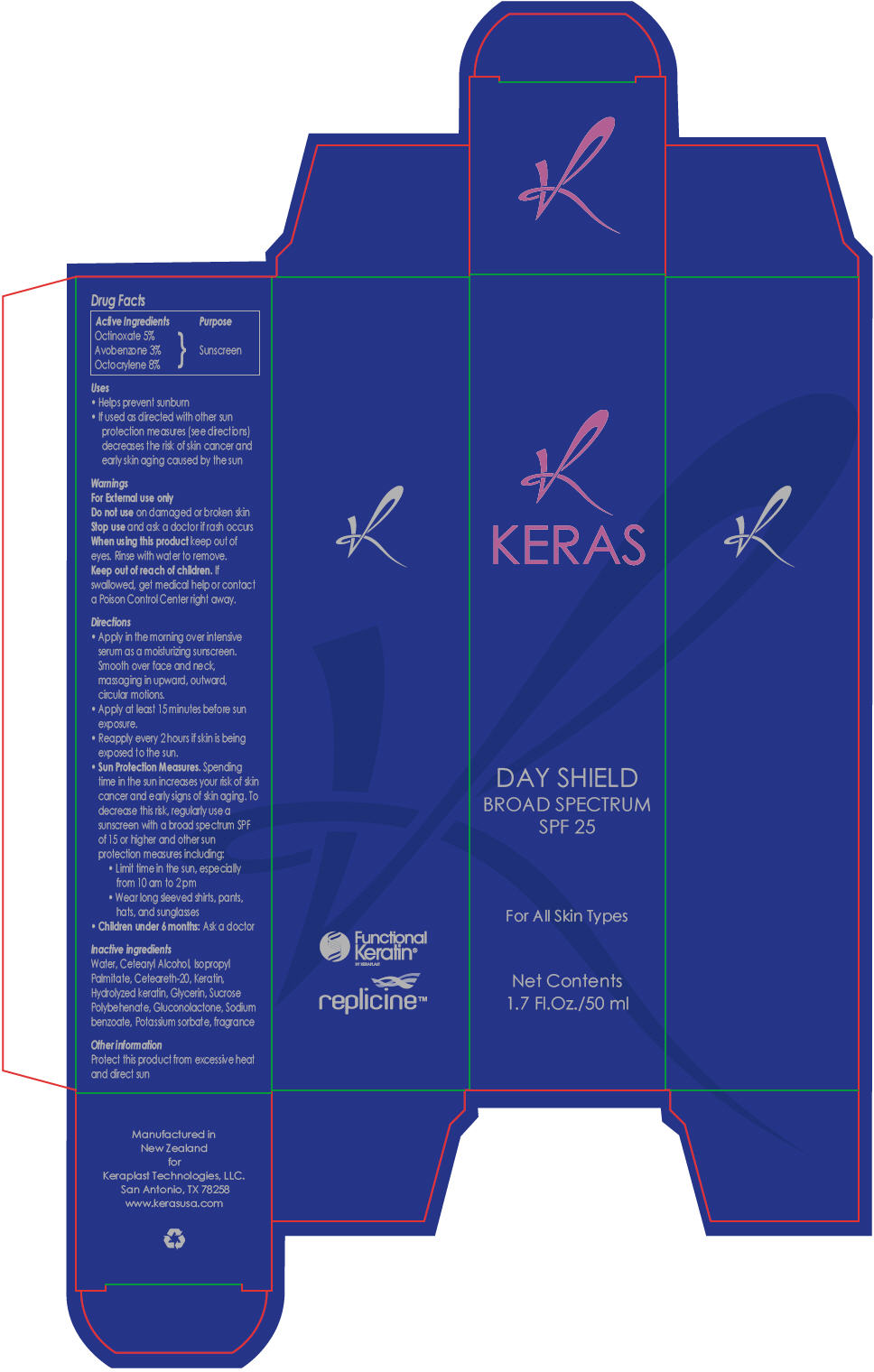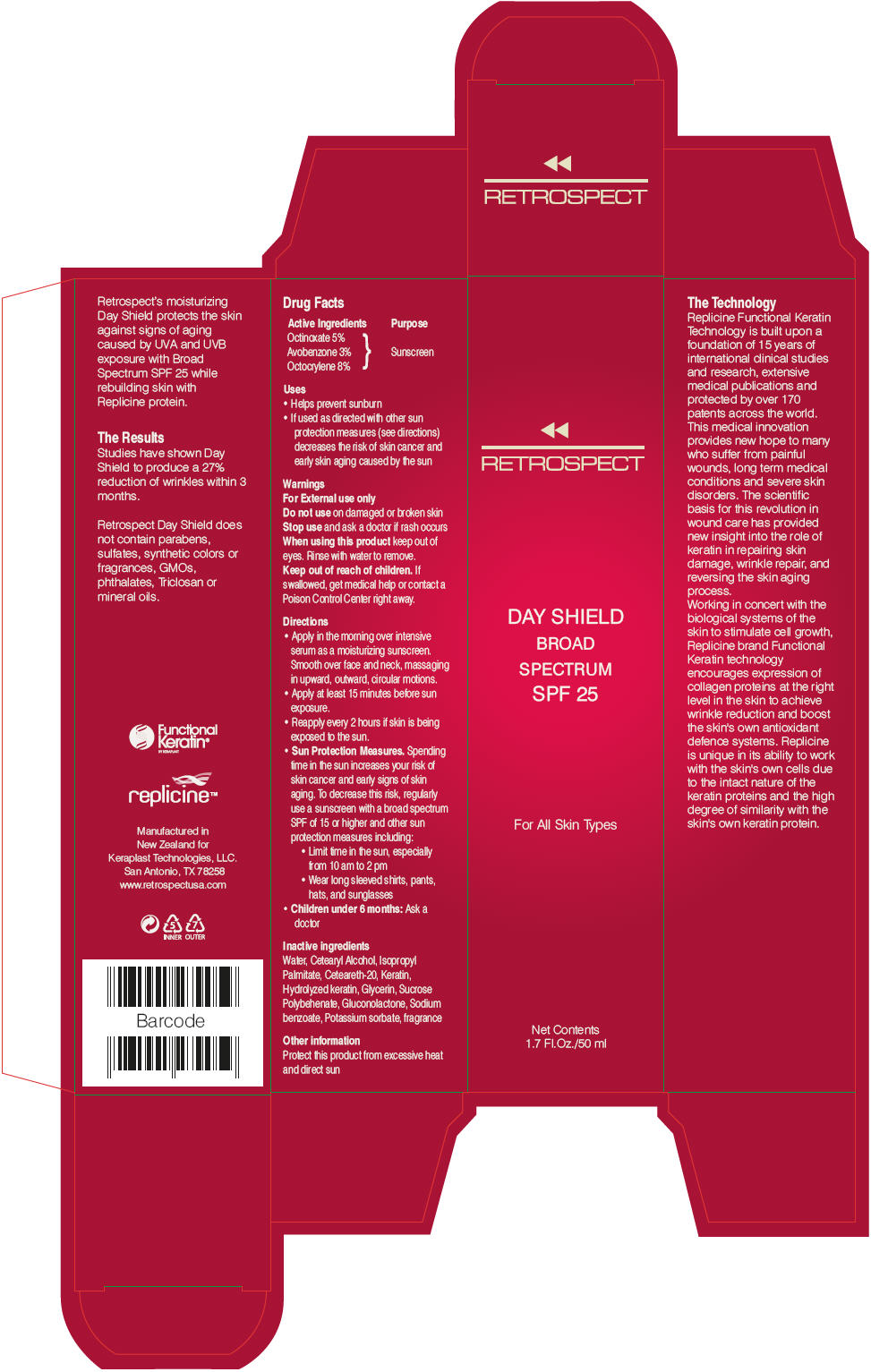 DRUG LABEL: keras day shield broad spectrum SPF 25
NDC: 24854-400 | Form: LOTION
Manufacturer: Keraplast Technologies LLC
Category: otc | Type: HUMAN OTC DRUG LABEL
Date: 20111130

ACTIVE INGREDIENTS: octinoxate 0.25 g/50 mL; avobenzone 0.15 g/50 mL; octocrylene 0.4 g/50 mL
INACTIVE INGREDIENTS: water; cetostearyl alcohol; isopropyl palmitate; polyoxyl 20 cetostearyl ether; glycerin; gluconolactone; sodium benzoate; potassium sorbate

Day Shield Broad Spectrum SPF 25

Drug Facts

Active Ingredients

Octinoxate 5%

Avobenzone 3%

Octocrylene 8%

Purpose

Sunscreen

Uses

- Helps prevent sunburn
- If used as directed with other sun protection measures (see directions) decreases the risk of skin cancer and early skin aging caused by the sun

Warnings

For External use only

Do not use on damaged or broken skin

Stop use and ask a doctor if rash occurs

When using this product keep out of eyes. Rinse with water to remove.

Keep out of reach of children. If swallowed, get medical help or contact a Poison Control Center right away.

Directions

- Apply in the morning over intensive serum as a moisturizing sunscreen. Smooth over face and neck, massaging in upward, outward, circular motions.
- Apply at least 15 minutes before sun exposure.
- Reapply every 2 hours if skin is being exposed to the sun.
- Sun Protection Measures. Spending time in the sun increases your risk of skin cancer and early signs of skin aging. To decrease this risk, regularly use a sunscreen with a broad spectrum SPF of 15 or higher and other sun protection measures including:
  - Limit time in the sun, especially from 10 am to 2 pm
  - Wear long sleeved shirts, pants, hats, and sunglasses
- Children under 6 months: Ask a doctor

Inactive ingredients

Water, Cetearyl Alcohol, Isopropyl Palmitate, Ceteareth-20, Keratin, Hydrolyzed keratin, Glycerin, Sucrose Polybehenate, Gluconolactone, Sodium benzoate, Potassium sorbate, fragrance

Other information

Protect this product from excessive heat and direct sun

Manufactured in
New Zealand
for
Keraplast Technologies, LLC.
San Antonio, TX 78258

PRINCIPAL DISPLAY PANEL - 50 ml Bottle Carton

K
KERAS

DAY SHIELD
BROAD SPECTRUM
SPF 25

For All Skin Types

Net Contents
1.7 Fl.Oz./50 ml

PRINCIPAL DISPLAY PANEL - 50 ml Bottle Carton

RETROSPECT

DAY SHIELD
BROAD
SPECTRUM
SPF 25

For All Skin Types

Net Contents
1.7 Fl.Oz./50 ml